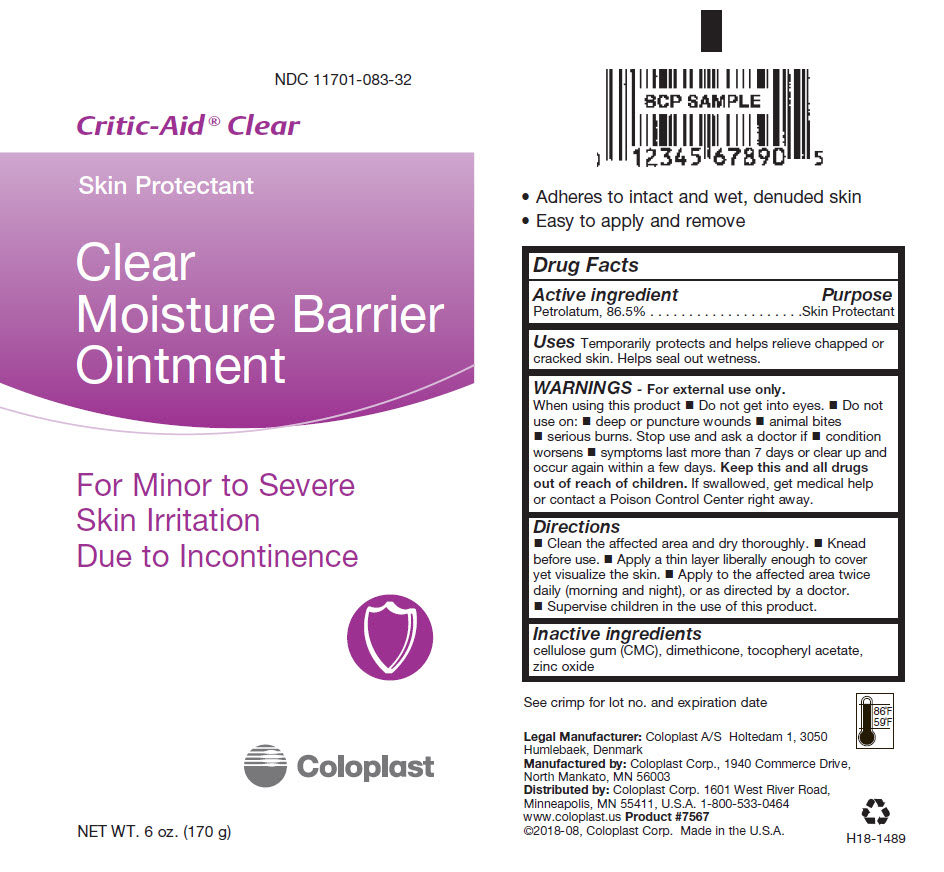 DRUG LABEL: Critic-Aid Clear
NDC: 11701-083 | Form: OINTMENT
Manufacturer: Coloplast Corp.
Category: otc | Type: HUMAN OTC DRUG LABEL
Date: 20241226

ACTIVE INGREDIENTS: Petrolatum 865 mg/1 g
INACTIVE INGREDIENTS: Zinc Oxide; .Alpha.-Tocopherol Acetate, DL-; CARBOXYMETHYLCELLULOSE SODIUM, UNSPECIFIED; Dimethicone 1000

Critic-Aid® Clear

Drug Facts

Active ingredient

Petrolatum, 86.5%

Purpose

Skin Protectant

Uses

Temporarily protects and helps relieve chapped or cracked skin. Helps seal out wetness.

WARNINGS

For external use only.

When using this product

- Do not get into eyes.

- Do not use on:
  - deep or puncture wounds
  - animal bites
  - serious burns.

Stop use and ask a doctor if

- condition worsens
- symptoms last more than 7 days or clear up and occur again within a few days.

KEEP OUT OF REACH OF CHILDREN

Keep this and all drugs out of reach of children. If swallowed, get medical help or contact a Poison Control Center right away.

Directions

- Clean the affected area and dry thoroughly.
- Knead before use.
- Apply a thin layer liberally enough to cover yet visualize the skin.
- Apply to the affected area twice daily (morning and night), or as directed by a doctor.
- Supervise children in the use of this product.

Inactive ingredients

cellulose gum (CMC), dimethicone, tocopheryl acetate, zinc oxide

Manufactured by: Coloplast Corp., 1940 Commerce Drive,
North Mankato, MN 56003

Distributed by: Coloplast Corp. 1601 West River Road,
Minneapolis, MN 55411, U.S.A.

PRINCIPAL DISPLAY PANEL - 170 g Tube Label

NDC 11701-083-32

Critic-Aid® Clear

Skin Protectant

Clear
Moisture Barrier
Ointment

For Minor to Severe
Skin Irritation
Due to Incontinence

Coloplast

NET WT. 6 oz. (170 g)